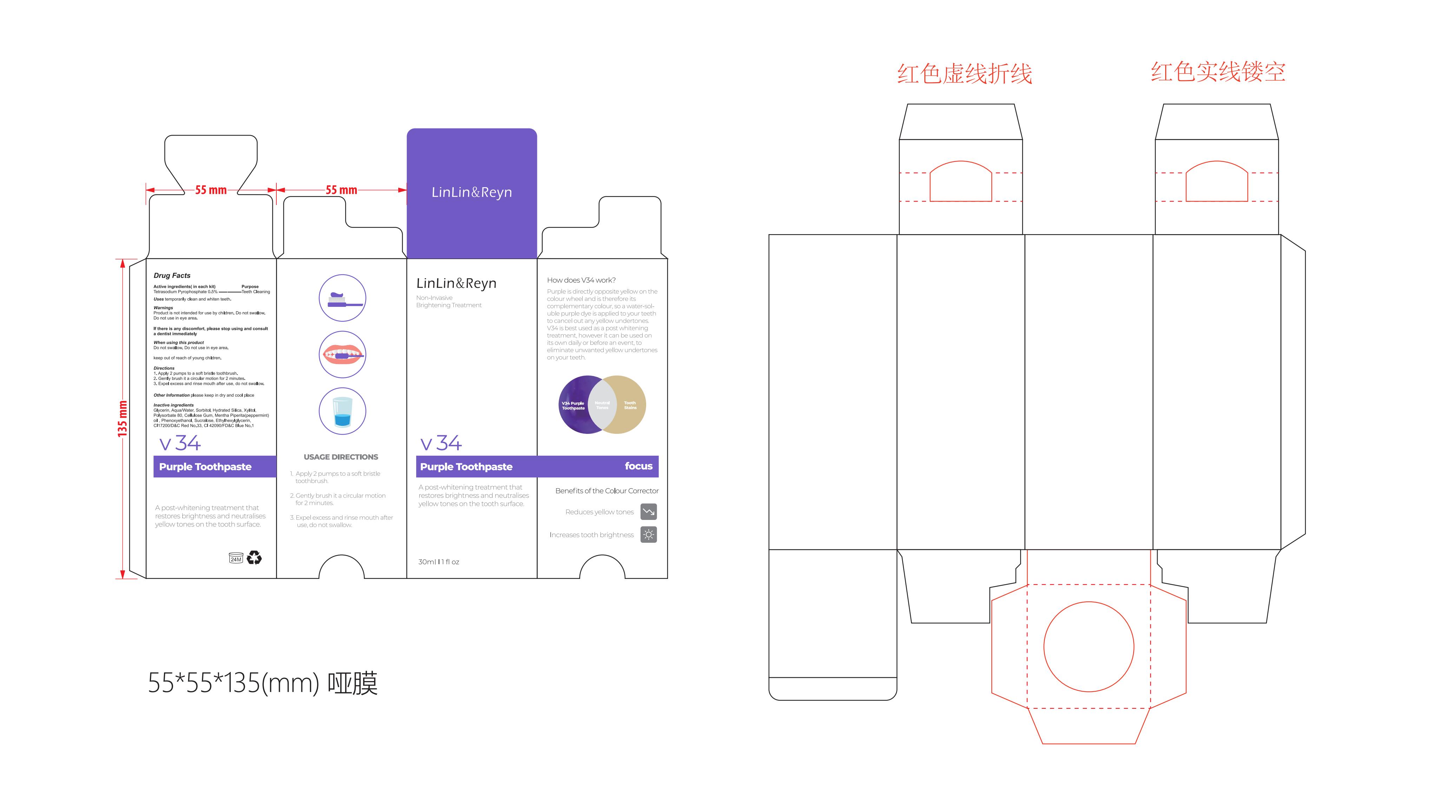 DRUG LABEL: V34 Colour Corrector
NDC: 83812-002 | Form: CREAM
Manufacturer: LLRN PERSONAL CARE(SHENZHEN)CO., LTD
Category: otc | Type: HUMAN OTC DRUG LABEL
Date: 20231123

ACTIVE INGREDIENTS: SODIUM PYROPHOSPHATE 0.5 g/100 mL
INACTIVE INGREDIENTS: GLYCERIN; WATER; PHENOXYETHANOL; FD&C BLUE NO. 1; CARBOXYMETHYLCELLULOSE SODIUM, UNSPECIFIED FORM; XYLITOL; POLYSORBATE 80; PEPPERMINT OIL; SUCRALOSE; D&C RED NO. 33; SORBITOL; HYDRATED SILICA; ETHYLHEXYLGLYCERIN

Active Ingredient

Tetrasodium Pyrophosphate 0.5%

Purpose

Teeth cleaning

Use

Those who want to clean and whiten their teeth.

Warnings

Product is not intended for use by children. Do not swallow. Do not use in eye area.

Do not use

Product is not intended for use by children.

When Using

Do not swallow. Do not use in eye area.

Stop Use

If there is any discomfort, please stop using.

Ask Doctor

If there is any discomfort, please consult a dentist immediately

Keep Oot Of Reach Of Children

keep out of reach of young children

Directions

1. Apply 2 pumps to a soft bristle toothbrush.
2. Gently brush it a circular motion for 2 minutes.
3. Expel excess and rinse mouth after use, do not swallow.

Other information

please keep in dry and cool place

Inactive ingredients

Glycerin、Aqua/Water、Sorbitol、Hydrated Silica、Xylitol、Polysorbate 80、Cellulose Gum、Mentha Piperita(peppermint) oil 、Phenoxyethanol、Sucralose、Ethylhexylglycerin、CI17200/D&C Red No.33、CI 42090/FD&C Blue No.1